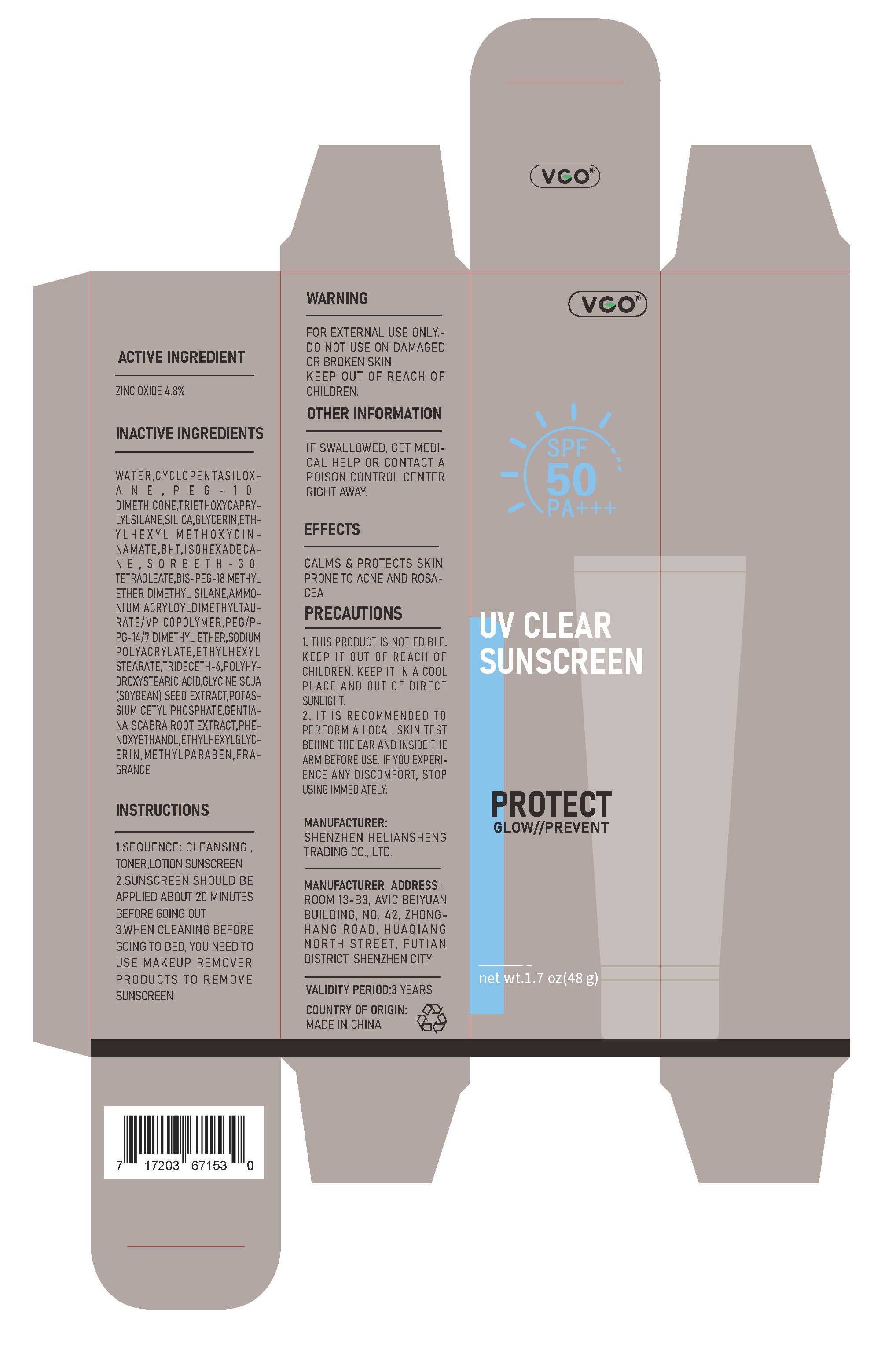 DRUG LABEL: VCO UV CLEAR SUNSCREEN
NDC: 84191-002 | Form: OINTMENT
Manufacturer: Shenzhen Heliansheng Trading Co., Ltd.
Category: otc | Type: HUMAN OTC DRUG LABEL
Date: 20240326

ACTIVE INGREDIENTS: ZINC OXIDE 4.8 g/100 g
INACTIVE INGREDIENTS: PEG/PPG-14/7 DIMETHYL ETHER; PEG-10 DIMETHICONE (200 CST); TRIETHOXYCAPRYLYLSILANE; SILICON DIOXIDE; ISOHEXADECANE; TRIDECETH-6; POLYHYDROXYSTEARIC ACID (2300 MW); CYCLOMETHICONE 5; ETHYLHEXYL STEARATE; GLYCERIN; WATER; OCTINOXATE; BIS-PEG-18 METHYL ETHER DIMETHYL SILANE; AMMONIUM ACRYLOYLDIMETHYLTAURATE/VP COPOLYMER; SODIUM POLYACRYLATE (8000 MW); SOYBEAN; GENTIANA SCABRA ROOT; METHYLPARABEN; BUTYLATED HYDROXYTOLUENE; POTASSIUM CETYL PHOSPHATE; PHENOXYETHANOL; ETHYLHEXYLGLYCERIN

84191-002

Active ingredient

ZINC OXIDE 4.8%

Purpose

Sunscreen

Use

helps prevent sunburn

higher SPF gives more sunburn protection

Warning

For external use only.

Do not use

on damaged or broken skin.

If Swallowed

Get medical help or contact a poison control center right away.

Directions

1.Sequence: Cleansing ,toner,lotion,sunscreen
2.Sunscreen should be applied about 20 minutes before going out
3.When cleaning before going to bed, you need to use makeup remover products to remove sunscreen

Inactive ingredients

Water, Cyclopentasiloxane, Peg-10 Dimethicone, Triethoxycaprylylsilane, Silica, Glycerin, Ethylhexyl Methoxycinnamate, Bht, Isohexadecane, Sorbeth-30 Tetraoleate, Bis-Peg-18 Methyl Ether Dimethyl Silane, Ammonium Acryloyldimethyltaurate/Vp Copolymer, Peg/Ppg-14/7 Dimethyl, Ether, Sodium Polyacrylate, Ethylhexyl Stearate, Trideceth-6, Polyhydroxystearic Acid, Glycine Soja (Soybean) Seed Extract, Potassium Cetyl Phosphate, Gentiana Scabra Root Extract, Phenoxyethanol, Ethylhexylglycerin, Methylparaben, Fragrance